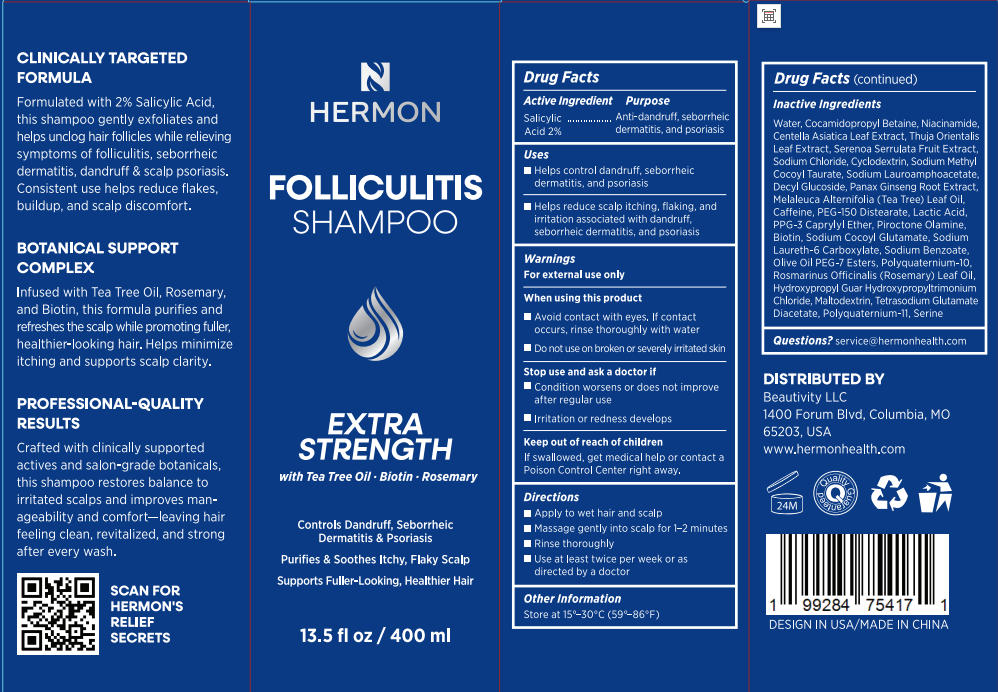 DRUG LABEL: Hermon Folliculitis Shampoo.
NDC: 85398-009 | Form: SHAMPOO
Manufacturer: Beautivity LLC
Category: otc | Type: HUMAN OTC DRUG LABEL
Date: 20250814

ACTIVE INGREDIENTS: SALICYLIC ACID 8 g/400 mL
INACTIVE INGREDIENTS: PIROCTONE OLAMINE; SERINE; BIOTIN; NIACINAMIDE; SODIUM BENZOATE; SAW PALMETTO; SODIUM LAUROAMPHOACETATE; SODIUM METHYL COCOYL TAURATE; DECYL GLUCOSIDE; PANAX GINSENG ROOT; MELALEUCA ALTERNIFOLIA (TEA TREE) LEAF OIL; CENTELLA ASIATICA; PLATYCLADUS ORIENTALIS LEAF; SODIUM CHLORIDE; PEG-150 DISTEARATE; SODIUM LAURETH-6 CARBOXYLATE; ROSMARINUS OFFICINALIS (ROSEMARY) LEAF OIL; COCAMIDOPROPYL BETAINE; PPG-10 CAPRYLYL ETHER; CYCLODEXTRIN; LACTIC ACID; WATER; TETRASODIUM GLUTAMATE DIACETATE; POLYQUATERNIUM-10 (1000 MPA.S AT 2%); MALTODEXTRIN; POLYQUATERNIUM-11 (1000000 MW); SODIUM COCOYL GLUTAMATE; HYDROXYPROPYL GUAR HYDROXYPROPYLTRIMONIUM CHLORIDE

Initial Drug Listing - Hermon Folliculitis Shampoo

ACTIVE INGREDIENT

Salicylic Acid 2%

PURPOSE

Anti-dandruff, seborrheicdermatitis, and psoriasis

DOSAGE AND ADMINISTRATION

- Helps control dandruff, seborrheic dermatitis, and psoriasis
- Helps reduce scalp itching, flaking, andirritation associated with dandruff, seborrheic dermatitis, and psoriasis

WARNINGS

For external use only

WHEN USING

- Avoid contact with eyes. lf contactoccurs, rinse thoroughly with water
- Do not use on broken or severely irritated skin

STOP USE

- Condition worsens or does not improve after regular use
- lrritation or redness develops

KEEP OUT OF REACH OF CHILDREN

If swallowed, get medical help or contact a Poison Control Center right away.

INDICATIONS AND USAGE

- Apply to wet hair and scalp
- Massage gently into scalp for 1-2 minutes
- Rinse thoroughly
- Use at least twice per week or as directed by a doctor

OTHER SAFETY INFORMATION

Store at 15°-30°C(59°-86°F)

INACTIVE INGREDIENT

Water, Cocamidopropyl Betaine, Niacinamide, Centella Asiatica Leaf Extract, Thuja Orientalis Leaf Extract, Serenoa Serrulata Fruit Extract,Sodium Chloride, Cyclodextrin, Sodium Methyl Cocoyl Taurate, Sodium Lauroamphoacetate, Decyl Glucoside, Panax Ginseng Root Extract,Melaleuca Alternifolia (Tea Tree) Leaf Oil.Caffeine, PEG-150 Distearate, Lactic Acid, PPG-3 Caprylyl Ether, Piroctone Olamine,Biotin, Sodium Cocoyl Glutamate, Sodium Laureth-6 Carboxylate, Sodium Benzoate,Olive Oil PEG-7 Esters, Polyquaternium-10.Rosmarinus Officinalis (Rosemary) Leaf Oil, Hydroxypropyl Guar HydroxypropyltrimoniumChloride,Maltodextrin,Tetrasodium Glutamate Diacetate, Polyquaternium-11. Serine

QUESTIONS

service@hermonhealth.com